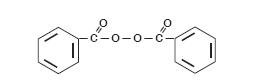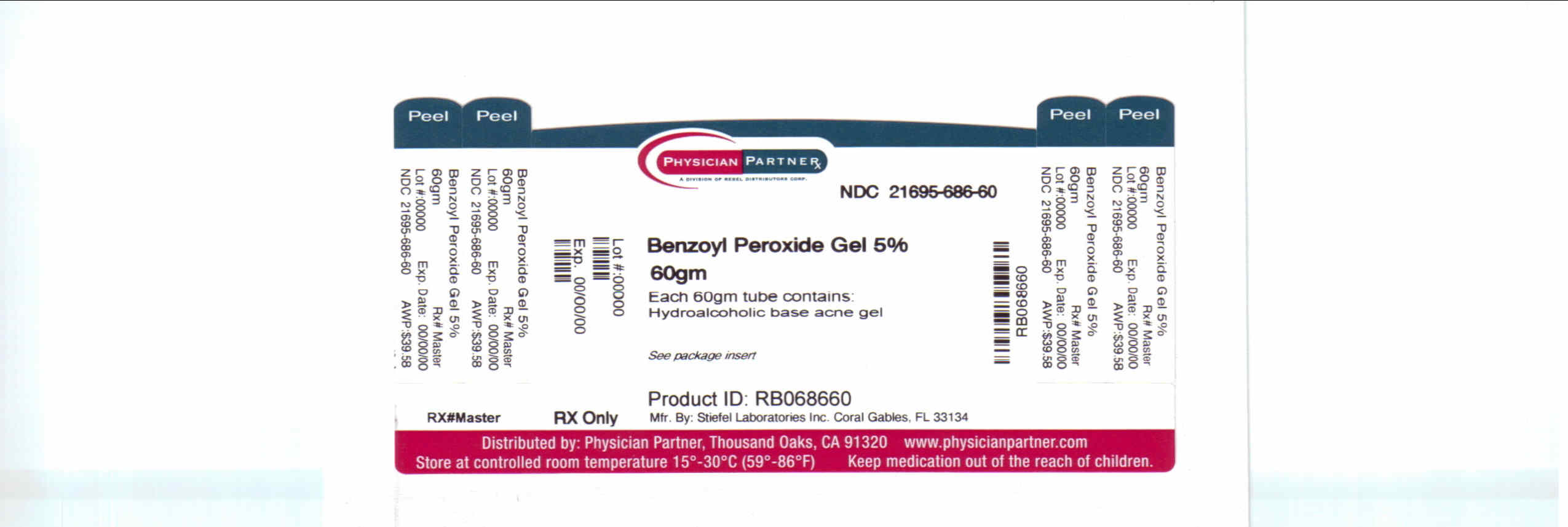 DRUG LABEL: Perrigo Benzoyl Peroxide
NDC: 21695-686 | Form: GEL
Manufacturer: Rebel Distributors Corp
Category: prescription | Type: HUMAN PRESCRIPTION DRUG LABEL
Date: 20110103

ACTIVE INGREDIENTS: BENZOYL PEROXIDE 5 g/100 g

BENZOYL PEROXIDE ALCOHOL BASE GEL, 5%

Benzoyl Peroxide Gel 5% Hydroalcoholic Base Acne Gel

Benzoyl Peroxide Gel 10% Hydroalcoholic Base Acne Gel

Rx Only

DESCRIPTION

Benzoyl Peroxide Gel 5% and 10% (Hydroalcoholic Base Acne Gels) are topical preparations containing benzoyl peroxide as the active ingredient.

Benzoyl Peroxide Gel 5% contains: 5% benzoyl peroxide in a hydroalcoholic gel base formulated with alcohol (12%, denatured with tert-butyl alcohol and denatonium benzoate), citric acid, disodium lauryl sulfosuccinate, hypromellose, laureth-12, magnesium aluminum silicate, and purified water. Benzoyl Peroxide Gel 10% contains: 10% benzoyl peroxide in a hydroalcoholic gel base formulated with alcohol (20%, denatured with tert-butyl alcohol and denatonium benzoate), citric acid, hypromellose, laureth-12, magnesium aluminum silicate, and purified water.

The structural formula of benzoyl peroxide is:

CLINICAL PHARMACOLOGY

The exact method of action of benzoyl peroxide in acne vulgaris is not known. Benzoyl peroxide is an antibacterial agent with demonstrated activity against Propionibacterium acnes. This action, combined with the mild keratolytic effect of benzoyl peroxide is believed to be responsible for its usefulness in acne. Benzoyl peroxide is absorbed by the skin where it is metabolized to benzoic acid and excreted as benzoate in the urine.

INDICATIONS AND USAGE

Benzoyl Peroxide Gel 5% and 10% are indicated for use in the topical treatment of mild to moderate acne vulgaris. Benzoyl Peroxide Gel 5% and 10% may be used as an adjunct in acne treatment regimens including antibiotics, retinoic acid products, and sulfur/salicylic acid containing preparations.

CONTRAINDICATIONS

Benzoyl Peroxide Gel 5% and 10% should not be used in patients who have shown hypersensitivity to benzoyl peroxide or to any of the other ingredients in the products.

PRECAUTIONS

General

For external use only. Avoid contact with eyes and mucous membranes. AVOID CONTACT WITH HAIR, FABRICS OR CARPETING AS BENZOYL PEROXIDE WILL CAUSE BLEACHING.

Carcinogenesis, Mutagenesis, Impairment of Fertility

Based upon all available evidence, benzoyl peroxide is not considered to be a carcinogen. However, data from a study using mice known to be highly susceptible to cancer suggest that benzoyl peroxide acts as a tumor promoter. The clinical significance of the findings is not known.

Pregnancy

Pregnancy Category C

Animal reproduction studies have not been conducted with benzoyl peroxide. It is also not known whether benzoyl peroxide can cause fetal harm when administered to a pregnant woman or can affect reproduction capacity. Benzoyl peroxide should be used by a pregnant woman only if clearly needed.

Nursing Mothers

It is not known whether this drug is excreted in human milk. Because many drugs are excreted in human milk, caution should be exercised when benzoyl peroxide is administered to a nursing woman.

Pediatric Use

Safety and effectiveness in children below the age of 12 have not been established.

ADVERSE REACTIONS

Contact sensitization reactions are associated with the use of topical benzoyl peroxide products and may be expected to occur in 10 to 25 of 1000 patients. The most frequent adverse reactions associated with benzoyl peroxide use are excessive erythema and peeling which may be expected to occur in 5 of 100 patients. Excessive erythema and peeling most frequently appear during the initial phase of drug use and may normally be controlled by reducing frequency of use.

DOSAGE AND ADMINISTRATION

It is recommended that therapy be initiated with Benzoyl Peroxide Gel 5%, applying the medication to the affected areas once a day during the first week, and twice a day thereafter as tolerated. Frequency of use should be adjusted to obtain the desired clinical response. Therapy with Benzoyl Peroxide Gel 10% may be initiated in patients who demonstrate accommodation to Benzoyl Peroxide Gel 5%.

Gentle cleansing of the affected areas prior to application of Benzoyl Peroxide Gel 5% or 10% may be beneficial.

Clinically visible improvements will normally occur by the third week of therapy. Maximum lesion reduction may be expected after approximately eight to twelve weeks of drug use. Continuing use of the drug is normally required to maintain a satisfactory clinical response.

HOW SUPPLIED

Benzoyl Peroxide Gel 5% (Hydroalcoholic Base Acne Gel) are supplied in 60 gram tubes.

Benzoyl Peroxide Gel 5% NDC 21695-686-60

STORAGE AND HANDLING

Store at 20°-25°C (68°-77°F) [see USP Controlled Room Temperature].

MANUFACTURED BY

STIEFEL LABORATORIES, INC.

CORAL GABLES, FL 33134

DISTRIBUTED BY

PERRIGO®

ALLEGAN, MI 49010

Rev. 10/08

302010

: 9X300 RC J2

Repackaged by:

REBEL DISTRIBUTORS CORP

Thousand Oaks, CA 91320